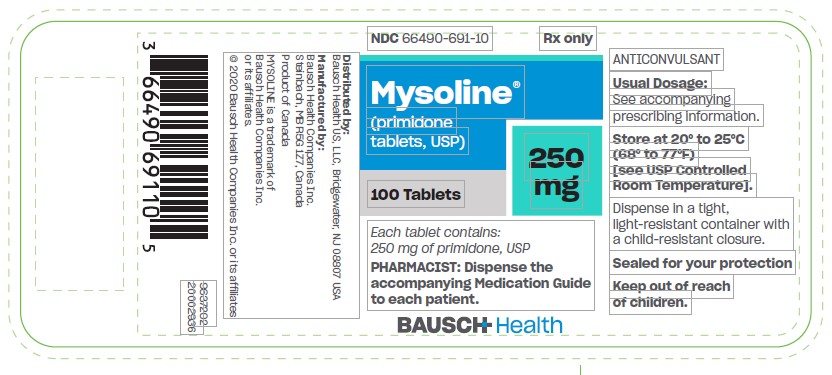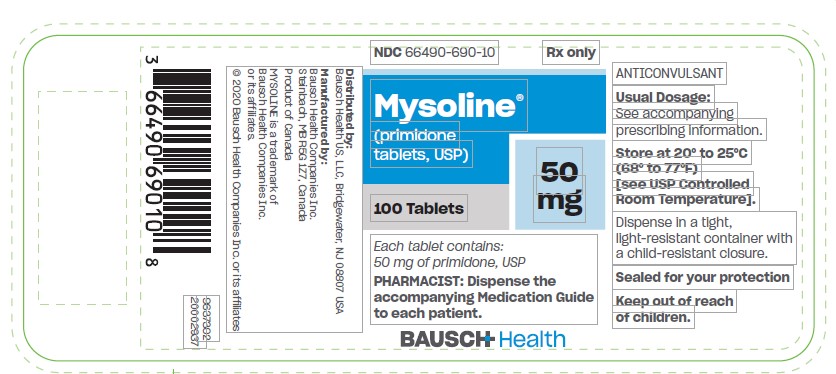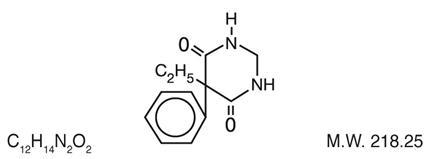 DRUG LABEL: Mysoline
NDC: 66490-690 | Form: TABLET
Manufacturer: Bausch Health US, LLC
Category: prescription | Type: HUMAN PRESCRIPTION DRUG LABEL
Date: 20200706

ACTIVE INGREDIENTS: Primidone 50 mg/1 1
INACTIVE INGREDIENTS: lactose Monohydrate; Magnesium stearate; WATER; sodium lauryl sulfate; sodium starch glycolate type a potato; talc; METHYLCELLULOSE (15 MPA.S); MICROCRYSTALLINE CELLULOSE

Mysoline® (primidone tablets, USP)
50 mg and 250 mg
Rx only
Anticonvulsant

DESCRIPTION

Chemical name: 5-ethyldihydro-5-phenyl-4,6 (1H, 5H)-pyrimidinedione. Structural formula:

MYSOLINE (primidone) is a white, crystalline, highly stable substance, M.P. 279-284°C. It is poorly soluble in water (60 mg per 100 mL at 37°C) and in most organic solvents. It possesses no acidic properties, in contrast to its barbiturate analog.

MYSOLINE 50 mg and 250 mg tablets contain the following inactive ingredients: lactose

monohydrate, NF; magnesium stearate, NF; methylcellulose, USP; microcrystalline cellulose, NF;

purified water, USP; sodium lauryl sulfate, NF; sodium starch glycolate, NF; and talc, USP.
MYSOLINE 250 mg tablets also contain ferric oxide yellow, NF.

_______________________________________________________________________________

ACTIONS

MYSOLINE raises electro- or chemoshock seizure thresholds or alters seizure patterns in experimental animals. The mechanism(s) of primidone’s antiepileptic action is not known.

Primidone per se has anticonvulsant activity as do its two metabolites, phenobarbital and phenylethylmalonamide (PEMA). In addition to its anticonvulsant activity, PEMA potentiates the anticonvulsant activity of phenobarbital in experimental animals.

INDICATIONS AND USAGE

MYSOLINE, used alone or concomitantly with other anticonvulsants, is indicated in the control of grand mal, psychomotor, and focal epileptic seizures. It may control grand mal seizures refractory to other anticonvulsant therapy.

CONTRAINDICATIONS

Primidone is contraindicated in: 1) patients with porphyria and 2) patients who are hypersensitive to phenobarbital (see ACTIONS).

WARNINGS

The abrupt withdrawal of antiepileptic medication may precipitate status epilepticus. The therapeutic efficacy of a dosage regimen takes several weeks before it can be assessed.

Suicidal Behavior and Ideation

Antiepileptic drugs (AEDs), including MYSOLINE, increase the risk of suicidal thoughts or behavior in patients taking these drugs for any indication. Patients treated with any AED for any indication should be monitored for the emergence or worsening of depression, suicidal thoughts or behavior, and/or any unusual changes in mood or behavior.

Pooled analyses of 199 placebo-controlled clinical trials (mono- and adjunctive therapy) of 11 different AEDs showed that patients randomized to one of the AEDs had approximately twice the risk (adjusted Relative Risk 1.8, 95% Cl:1.2, 2.7) of suicidal thinking or behavior compared to patients randomized to placebo. In these trials, which had a median treatment duration of 12 weeks, the estimated incidence rate of suicidal behavior or ideation among 27,863 AED-treated patients was 0.43%, compared to 0.24% among 16,029 placebo-treated patients, representing an increase of approximately one case of suicidal thinking or behavior for every 530 patients treated. There were four suicides in drug-treated patients in the trials and none in placebo-treated patients, but the number is too small to allow any conclusion about drug effect on suicide.

The increased risk of suicidal thoughts or behavior with AEDs was observed as early as 1 week after starting drug treatment with AEDs and persisted for the duration of treatment assessed. Because most trials included in the analysis did not extend beyond 24 weeks, the risk of suicidal thoughts or behavior beyond 24 weeks could not be assessed.

The risk of suicidal thoughts or behavior was generally consistent among drugs in the data analyzed. The finding of increased risk with AEDs of varying mechanisms of action and across a range of indications suggests that the risk applies to all AEDs used for any indication. The risk did not vary substantially by age (5 to 100 years) in the clinical trials analyzed.

Table 1 shows absolute and relative risk by indication for all evaluated AEDs.

Table 1: Risk by indication for antiepileptic drugs in the pooled analysis
Indication | Placebo Patients with Events Per 1000 Patients | Drug Patients with Events Per 1000 Patients | Relative Risk: Incidence of Events in Drug Patients/ Incidence in Placebo Patients | Risk Difference: Additional Drug Patients with Events Per 1000 Patients
Epilepsy | 1.0 | 3.4 | 3.5 | 2.4
Psychiatric | 5.7 | 8.5 | 1.5 | 2.9
Other | 1.0 | 1.8 | 1.9 | 0.9
Total | 2.4 | 4.3 | 1.8 | 1.9

The relative risk for suicidal thoughts or behavior was higher in clinical trials for epilepsy than in clinical trials for psychiatric or other conditions, but the absolute risk differences were similar for the epilepsy and psychiatric indications.

Anyone considering prescribing MYSOLINE or any other AED must balance the risk of suicidal thoughts or behavior with the risk of untreated illness. Epilepsy and many other illnesses for which AEDs are prescribed are themselves associated with morbidity and mortality and an increased risk of suicidal thoughts and behavior. Should suicidal thoughts and behavior emerge during treatment, the prescriber needs to consider whether the emergence of these symptoms in any given patient may be related to the illness being treated.

Patients, their caregivers, and families should be informed that AEDs increase the risk of suicidal thoughts and behavior and should be advised of the need to be alert for the emergence or worsening of the signs and symptoms of depression, any unusual changes in mood or behavior, or the emergence of suicidal thoughts, behavior, or thoughts about self-harm. Behaviors of concern should be reported immediately to healthcare providers.

Pregnancy

To provide information regarding the effects of in utero exposure to MYSOLINE, physicians are advised to recommend that pregnant patients taking MYSOLINE enroll in the North American Antiepileptic Drug (NAAED) Pregnancy Registry. This can be done by calling the toll-free number 1-888-233-2334, and must be done by patients themselves. Information on the registry can also be found at the website http://www.aedpregnancyregistry.org/.

The effects of MYSOLINE in human pregnancy and nursing infants are unknown.

Recent reports suggest an association between the use of anticonvulsant drugs by women with epilepsy and an elevated incidence of birth defects in children born to these women. Data are more extensive with respect to diphenylhydantoin and phenobarbital, but these are also the most commonly prescribed anticonvulsants; less systematic or anecdotal reports suggest a possible similar association with the use of all known anticonvulsant drugs.

The reports suggesting an elevated incidence of birth defects in children of drug-treated epileptic women cannot be regarded as adequate to prove a definite cause-and-effect relationship.

There are intrinsic methodologic problems in obtaining adequate data on drug teratogenicity in humans; the possibility also exists that other factors leading to birth defects, e.g., genetic factors or the epileptic condition itself, may be more important than drug therapy. The great majority of mothers on anticonvulsant medication deliver normal infants. It is important to note that anticonvulsant drugs should not be discontinued in patients in whom the drug is administered to prevent major seizures because of the strong possibility of precipitating status epilepticus with attendant hypoxia and threat to life. In individual cases where the severity and frequency of the seizure disorders are such that the removal of medication does not pose a serious threat to the patient, discontinuation of the drug may be considered prior to and during pregnancy, although it cannot be said with any confidence that even minor seizures do not pose some hazard to the developing embryo or fetus.

The prescribing physician will wish to weigh these considerations in treating or counseling epileptic women of childbearing potential. Neonatal hemorrhage, with a coagulation defect resembling vitamin K deficiency, has been described in newborns whose mothers were taking primidone and other anticonvulsants. Pregnant women under anticonvulsant therapy should receive prophylactic vitamin K1 therapy for 1 month prior to, and during, delivery.

PRECAUTIONS

The total daily dosage should not exceed 2 g. Since MYSOLINE therapy generally extends over prolonged periods, a complete blood count and a sequential multiple analysis-12 (SMA-12) test should be made every 6 months.

Nursing Mothers

There is evidence in mothers treated with primidone that the drug appears in breast milk in substantial quantities. Since tests for the presence of primidone in biological fluids are too complex to be carried out in the average clinical laboratory, it is suggested that the presence of undue somnolence and drowsiness in nursing newborns of MYSOLINE-treated mothers be taken as an indication that nursing should be discontinued.

Information for Patients

Suicidal Thoughts and Behavior
Patients, their caregivers, and families should be counseled that AEDs, including MYSOLINE, may increase the risk of suicidal thoughts and behavior and should be advised of the need to be alert for the emergence or worsening of symptoms of depression, any unusual changes in mood or behavior, or the emergence of suicidal thoughts, behavior, or thoughts about self-harm. Behaviors of concern should be reported immediately to healthcare providers.

Pregnancy

Patients should be encouraged to enroll in the NAAED Pregnancy Registry if they become pregnant. This registry is collecting information about the safety of antiepileptic drugs during pregnancy. To enroll, patients can call the toll-free number 1-888-233-2334 (see WARNINGS, Pregnancy). Please refer to the MYSOLINE Medication Guide provided with the product for more information.

ADVERSE REACTIONS

The most frequently occurring early side effects are ataxia and vertigo. These tend to disappear with continued therapy, or with reduction of initial dosage. Occasionally, the following have been reported: nausea, anorexia, vomiting, fatigue, hyperirritability, emotional disturbances, sexual impotency, diplopia, nystagmus, drowsiness, and morbilliform skin eruptions. Granulocytopenia, agranulocytosis, and red-cell hypoplasia and aplasia, have been reported rarely. These and, occasionally, other persistent or severe side effects may necessitate withdrawal of the drug. Megaloblastic anemia may occur as a rare idiosyncrasy to MYSOLINE and to other anticonvulsants. The anemia responds to folic acid without necessity of discontinuing medication.

To report SUSPECTED ADVERSE REACTIONS, contact Bausch Health US, LLC at 1-800-321-4576 or FDA at 1-800-FDA-1088 or www.fda.gov/medwatch.

DOSAGE AND ADMINISTRATION

Usual Dosage

Patients 8 years of age and older who have received no previous treatment may be started on MYSOLINE according to the following regimen using either 50 mg or scored 250 mg MYSOLINE tablets:

Days 1 to 3: 100 to 125 mg at bedtime.
Days 4 to 6: 100 to 125 mg twice a day.
Days 7 to 9: 100 to 125 mg three times a day.
Day 10 to maintenance: 250 mg three times a day.

For most adults and children 8 years of age and over, the usual maintenance dosage is three to four 250 mg MYSOLINE tablets in divided doses (250 mg three times a day or four times a day). If required, an increase to five or six 250 mg tablets daily may be made, but daily doses should not exceed 500 mg four times a day.

Dosage should be individualized to provide maximum benefit. In some cases, serum blood level determinations of primidone may be necessary for optimal dosage adjustment. The clinically effective serum level for primidone is between 5 to 12 mcg/mL.

INITIAL: ADULTS AND CHILDREN OVER 8
KEY: •=50 mg tablet; ●=250 mg tablet
DAY | 1 | 2 | 3 | 4 | 5 | 6
AM |  |  |  | •• | •• | ••
NOON
PM | •• | •• | •• | •• | •• | ••
DAY | 7 | 8 | 9 | 10 | 11 | 12
AM | •• | •• | •• | ● | Adjust to Maintenance
NOON | •• | •• | •• | ● | Adjust to Maintenance
PM | •• | •• | •• | ● | Adjust to Maintenance

Patients Already Receiving Other Anticonvulsants

MYSOLINE should be started at 100 to 125 mg at bedtime and gradually increased to maintenance level as the other drug is gradually decreased. This regimen should be continued until satisfactory dosage level is achieved for the combination, or the other medication is completely withdrawn. When therapy with MYSOLINE alone is the objective, the transition from concomitant therapy should not be completed in less than 2 weeks.

Pediatric Dosage

For children under 8 years of age, the following regimen may be used:

Days 1 to 3: 50 mg at bedtime.
Days 4 to 6: 50 mg twice a day.
Days 7 to 9: 100 mg twice a day.
Day 10 to maintenance: 125 mg three times a day to 250 mg three times a day.

For children under 8 years of age, the usual maintenance dosage is 125 to 250 mg three times daily or, 10 to 25 mg/kg/day in divided doses.

HOW SUPPLIED

MYSOLINE Tablets

Modified square, flat faced, beveled edge, compressed light yellow color tablet. One face is debossed (impressed) with “MYSOLINE” and “250” that are divided by a debossed bisect line. The opposite side is embossed with the letter “M”, in bottles of 100 (NDC 66490-691-10).

Modified square, flat faced, beveled edge, compressed white color tablet. One face is debossed (impressed) with “MYSOLINE” and “50” that are divided by a debossed bisect line. The opposite side is embossed with the letter “M”, in bottles of 100 (NDC 66490-690-10).

Storage

Store at 20° to 25°C (68° to 77°F)
[see USP Controlled Room Temperature].

Dispense in a tight, light-resistant container with a child-resistant closure.

Distributed by:
Bausch Health US, LLC
Bridgewater, NJ 08807 USA

Manufactured by:

Bausch Health Companies Inc.
Steinbach, MB R5G 1Z7, Canada

MYSOLINE is a trademark of Bausch Health Companies Inc. or its affiliates.

© 2020 Bausch Health Companies Inc. or its affiliates

Rev. 07/2020
  9648502 20002938

MEDICATION GUIDE

MYSOLINE (My-so-lean)
(primidone tablets, USP), 50 mg and 250 mg

Read this Medication Guide before you start taking MYSOLINE and each time you get a refill. There may be new information. This information does not take the place of talking to your healthcare provider about your medical condition or treatment.

What is the most important information I should know about MYSOLINE?

Like other antiepileptic drugs, MYSOLINE may cause suicidal thoughts or actions in a very small number of people, about 1 in 500.

Call a healthcare provider right away if you have any of these symptoms, especially if they are new, worse, or worry you:

- thoughts about suicide or dying
- attempts to commit suicide
- new or worsening depression
- new or worsening anxiety
- feeling agitated or restless
- panic attacks
- trouble sleeping (insomnia)
- new or worsening irritability
- acting aggressive, being angry, or violent
- acting on dangerous impulses
- an extreme increase in activity and talking (mania)
- other unusual changes in behavior or mood
Do not stop taking MYSOLINE without first talking to a healthcare provider.
- Stopping MYSOLINE suddenly can cause serious problems. Stopping a seizure medicine suddenly in a patient who has epilepsy can cause seizures that will not stop (status epilepticus).

Suicidal thoughts or actions can be caused by things other than medicines. If you have suicidal thoughts or actions, your healthcare provider may check for other causes.

How can I watch for early symptoms of suicidal thoughts and actions?

- Pay attention to any changes, especially sudden changes, in mood, behaviors, thoughts, or feelings.
- Keep all follow-up visits with your healthcare provider as scheduled.
- Call your healthcare provider between visits as needed, especially if you are worried about symptoms.

What is MYSOLINE?

MYSOLINE is a prescription medicine used alone or with other medicines to treat people with:

- generalized tonic-clonic (grand mal) seizures
- complex partial (psychomotor) seizures
- partial (focal) epileptic seizures

Who should not take MYSOLINE?

Do not take MYSOLINE if you:

- have a genetic disorder called porphyria
- are allergic to phenobarbital

What should I tell my healthcare provider before taking MYSOLINE?

Before you take MYSOLINE, tell your healthcare provider if you:

- have or have had depression, mood problems, or suicidal thoughts or behavior
- have any other medical conditions
- are pregnant or planning to become pregnant. MYSOLINE may harm your unborn baby. Tell your healthcare provider right away if you become pregnant while taking MYSOLINE. You and your healthcare provider will decide if you should take MYSOLINE while you are pregnant.
  - If you become pregnant while taking MYSOLINE, talk to your healthcare provider about registering with the North American Antiepileptic Drug (NAAED) Pregnancy Registry. You can enroll in this registry by calling 1-888-233-2334. The purpose of this registry is to collect information about the safety of antiepileptic drugs during pregnancy.
- are breastfeeding or plan to breastfeed. MYSOLINE can pass into breast milk. Talk to your healthcare provider about the best way to feed your baby if you take MYSOLINE.

Tell your healthcare provider about all the medicines you take, including prescription and nonprescription medicines, vitamins, and herbal supplements. Taking MYSOLINE with certain other medicines can cause side effects or affect how well they work. Do not start or stop other medicines without talking to your healthcare provider.

Know the medicines you take. Keep a list of them and show it to your healthcare provider and pharmacist each time you get a new medicine.

How should I take MYSOLINE?

Take MYSOLINE exactly as prescribed. Your healthcare provider will tell you how much MYSOLINE to take and when to take it.

- Your healthcare provider may change your dose. Do not change your dose without talking to your healthcare provider.
- Do not stop taking MYSOLINE without first talking to your healthcare provider. Stopping MYSOLINE suddenly can cause serious problems.
- If you take too much MYSOLINE, call your healthcare provider or local Poison Control Center right away.

What should I avoid while taking MYSOLINE?

- MYSOLINE can make you sleepy or dizzy. Do not drink alcohol or take other drugs that make you sleepy or dizzy while taking MYSOLINE without first discussing this with your healthcare provider. Taking MYSOLINE with alcohol or drugs that cause sleepiness or dizziness may make your sleepiness or dizziness worse.
- Do not drive, operate heavy machinery, or do other dangerous activities until you know how MYSOLINE affects you. MYSOLINE can slow your thinking and motor skills.

What are the possible side effects of MYSOLINE?

See “What is the most important information I should know about MYSOLINE?”

MYSOLINE may cause other serious side effects including:

- Sleepiness that can be severe, especially when you first start taking MYSOLINE.
- MYSOLINE may rarely cause blood problems. Symptoms may include:
  - fever, swollen glands, or sore throat that come and go or do not go away
  - frequent infections or an infection that does not go away
  - tiredness
  - shortness of breath
- MYSOLINE may rarely cause allergic reactions. Symptoms may include:
  - skin rash
  - hives
  - sores in your mouth
  - blistering or peeling skin

The most common side effects of MYSOLINE include:

- problems with walking and moving
- feelings of dizziness, spinning, or swaying (vertigo)

These are not all the possible side effects of MYSOLINE. For more information, ask your healthcare provider or pharmacist.

Tell your healthcare provider if you have any side effect that bothers you or that does not go away.

Call your doctor for medical advice about side effects. You may report side effects to FDA at 1-800-FDA-1088.

How should I store MYSOLINE?

Store MYSOLINE at room temperature between 68° to 77°F (20° to 25°C) in a tight, light-resistant container.

Keep MYSOLINE and all medicines out of reach of children.

General Information about MYSOLINE

Medicines are sometimes prescribed for purposes other than those listed in a Medication Guide. Do not use MYSOLINE for a condition for which it was not prescribed. Do not give MYSOLINE to other people, even if they have the same symptoms that you have. It may harm them.

This Medication Guide summarizes the most important information about MYSOLINE. If you would like more information, talk with your healthcare provider. You can ask your pharmacist or healthcare provider for information about MYSOLINE that is written for health professionals.

For more information, go to www.bauschhealth.com or call 1-800-321-4576.

What are the ingredients in MYSOLINE?

Active Ingredient: primidone, USP

Inactive Ingredients: lactose monohydrate, NF; magnesium stearate, NF;

methylcellulose, USP; microcrystalline cellulose, NF; purified water, USP; sodium lauryl

sulfate, NF; sodium starch glycolate, NF; and talc, USP.

MYSOLINE 250 mg tablets also contain ferric oxide yellow, NF.

Distributed by:
Bausch Health US, LLC
Bridgewater, NJ 08807 USA

Manufactured by:
Bausch Health Companies Inc.
Steinbach, MB R5G 1Z7, Canada

MYSOLINE is a trademark of Bausch Health Companies Inc. or its affiliates.

© 2020 Bausch Health Companies Inc. or its affiliates

This Medication Guide has been approved by the U.S. Food and Drug Administration.

Rev. 07/2020

9648502 20002938

PRINCIPAL DISPLAY PANEL - 250 mg Tablet Bottle Label

NDC 66490-691-10

Rx Only

Mysoline®
(primidone tablets, USP)

250 mg

100 Tablets

Each tablet
contains 250 mg
of primidone, USP

PHARMACIST: Dispense the accompanying
Medication Guide to each patient.

BAUSCH Health

PRINCIPAL DISPLAY PANEL - 50 mg Tablet Bottle Label

NDC 66490-690-10

Rx Only

Mysoline®
(primidone tablets, USP)

50 mg
100 Tablets

Each tablet
contains 50 mg
of primidone, USP

PHARMACIST: Dispense the accompanying
Medication Guide to each patient.

BAUSCH Health